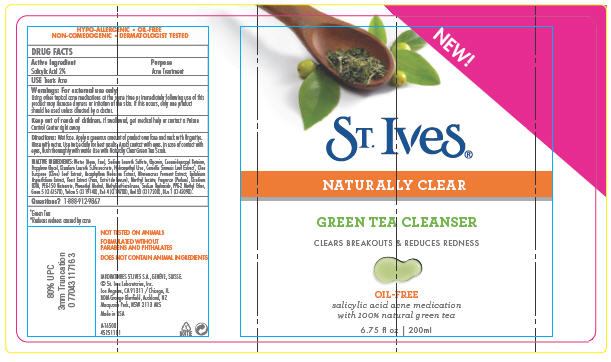 DRUG LABEL: St. Ives 
NDC: 12488-0400 | Form: SOAP
Manufacturer: Alberto-Culver USA Inc.
Category: otc | Type: HUMAN OTC DRUG LABEL
Date: 20100108

ACTIVE INGREDIENTS: Salicylic Acid 0.02 mL/1 mL
INACTIVE INGREDIENTS: Water; D&C Red No. 33; Fd&C Red No. 4; Fd&C Blue No. 1; Fd&C Yellow No. 5; D&C Green No. 5; Edetate Disodium; Sodium Laureth Sulfate; Cocamidopropyl Betaine; Propylene Glycol; Sodium Hydroxide; Disodium Laureth Sulfosuccinate; Menthyl Lactate; Glycerin; Phenethyl Alcohol; Green Tea Leaf

ST. Ives®
NATURALLY CLEAR
GREEN TEA CLEANSER

DRUG FACTS

Active Ingredient

Salicylic Acid 2%

Purpose

Acne Treatment

USE

Treats Acne

Warnings

For external use only.

WHEN USING

Using other topical acne medications at the same time or immediately following use of this product may increase dryness or irritation of the skin. If this occurs, only one product should be used unless directed by a doctor.

Keep out of reach of children. If swallowed, get medical help or contact a Poison Control Center right away.

Directions

Wet face. Apply a generous amount of product over face and neck with fingertips. Rinse with water. Use twice daily for best results. Avoid contact with eyes. In case of contact with eyes, flush thoroughly with water. Use with Naturally Clear Green Tea Scrub.

INACTIVE INGREDIENTS

Water (Aqua, Eau), Sodium Laureth Sulfate, Glycerin, Cocamidopropyl Betaine, Propylene Glycol, Disodium Laureth Sulfosuccinate, Hydroxyethyl Urea, Camellia Sinensis Leaf Extract [Green Tea] , Olea Europaea (Olive) Leaf Extract, Ascophyllum Nodosum Extract, Alteromonas Ferment Extract, Epilobium Angustifolium Extract, Yeast Extract (Faex, Extrait de Levure), Menthyl Lactate, Fragrance (Parfum), Disodium EDTA, PEG-150 Distearate, Phenethyl Alcohol, Methylisothiazolinone, Sodium Hydroxide, PPG-2 Methyl Ether, Green 5 (CI 61570), Yellow 5 (CI 19140), Red 4 (CI 14700), Red 33 (CI 17200), Blue 1 (CI 42090).

Questions?

1-888-912-9867

PRINCIPAL DISPLAY PANEL - 200 mL Bottle Label

NEW!

ST. Ives®

NATURALLY CLEAR

GREEN TEA CLEANSER

CLEARS BREAKOUTS & REDUCES REDNESS

OIL-FREE
salicylic acid acne medication
with 100% natural green tea

6.75 fl oz | 200ml